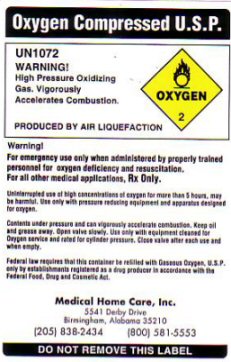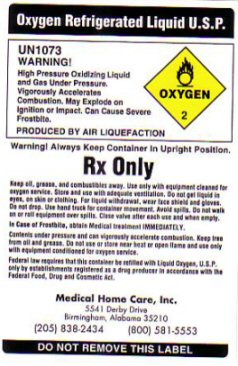 DRUG LABEL: OXYGEN
NDC: 62000-321 | Form: GAS
Manufacturer: Medical Home Care, Inc
Category: prescription | Type: HUMAN PRESCRIPTION DRUG LABEL
Date: 20100101

ACTIVE INGREDIENTS: OXYGEN 99.6 L/100 L

OXYGEN COMPRESSED LABEL

OXYGEN COMPRESSED U.S.P. UN 1072 WARNING! HIGH PRESSURE OXIDIZING GAS. VIGOROUSLY ACCELERATES COMBUSTION - OXYGEN - 2 - PRODUCED BY AIR LIQUEFACTION. UNINTERRUPTED USE OF HIGH CONCENTRATIONS OF OXYGEN FOR MORE THAN 5 HOURS, MAY BE HARMFUL. USE ONLY WITH PRESSURE REDUCING EQUIPMENT AND APPARATUS DESIGNED FOR OXYGEN. CONTENTS UNDER PRESSURE AND CAN VIGOROUSLY ACCELERATE COMBUSTION. KEEP OIL AND GREASE AWAY. OPEN VALVE SLOWLY. USE ONLY WITH EQUIPMENT CLEANED FOR OXYGEN SERVICE AND RATED FOR CYLINDER PRESSURE. CLOSE VALVE AFTER EACH USE AND WHEN EMPTY.

OXYGEN REFRIGERATED LIQUID LABEL

OXYGEN REFRIGERATED LIQUID U.S.P. UN 1073 WARNING! HIGH PRESSURE OXIDIZING LIQUID AND GAS UNDER PRESSURE. VIGOROUSLY ACCELERATES COMBUSTION. MAY EXPLODE ON IGNITION OR IMPACT. CAN CAUSE SEVERE FROSTBITE. PRODUCED BY AIR LIQUEFACTION. OXYGEN - 2

WARNING! ALWAYS KEEP CONTAINER IN UPRIGHT POSITION. Rx ONLY

KEEP OIL GREASE AND COMBUSTIBLES AWAY. USE ONLY WITH EQUIPMENT CLEANED FOR OXYGEN SERVICE. STORE AND USE WITH ADEQUATE VENTILATION. DO NOT GET LIQUID IN EYES, ON SKIN OR CLOTHING. FOR LIQUID WITHDRAWAL, WEAR FACE SHIELD AND GLOVES. DO NOT DROP. USE HAND TRUCK FOR CONTAINER MOVEMENT. AVOID SPILLS DO NOT WALK OR ROLL EQUIPMENT OVER SPILLS. CLOSE VALVE AFTER EACH USE AND WHEN EMPTY. IN CASE OF FROSTBITE OBTAIN MEDICAL TREATMENT IMMEDIATELY. CONTENTS UNDER PRESSURE AND CAN VIGOROUSLY ACCELERATE COMBUSTION. KEEP FREE OF OIL AND GREASE. DO NOT USE OR STORE NEAR HEAT OR OPEN FLAME AND USE ONLY WITH EQUIPMENT CONDITIONED FOR OXYGEN SERVICE.

GENERAL WARNINGS AND PRECAUTIONS

FOR EMERGENCY USE ONLY WHEN ADMINISTERED BY PROPERLY TRAINED PERSONNEL FOR OXYGEN DEFICIENCY AND RESUSCITATION. FOR ALL OTHER MEDICAL APPLICATIONS Rx ONLY. FEDERAL LAW REQUIRES THAT THIS CONTAINER BE REFILLED WITH OXYGEN U.S.P. ONLY BY ESTABLISHMENTS REGISTERED AS A DRUG PRODUCER IN ACCORDANCE WITH THE FEDERAL FOOD, DRUG AND COSMETIC ACT.

DO NOT REMOVE THIS LABEL